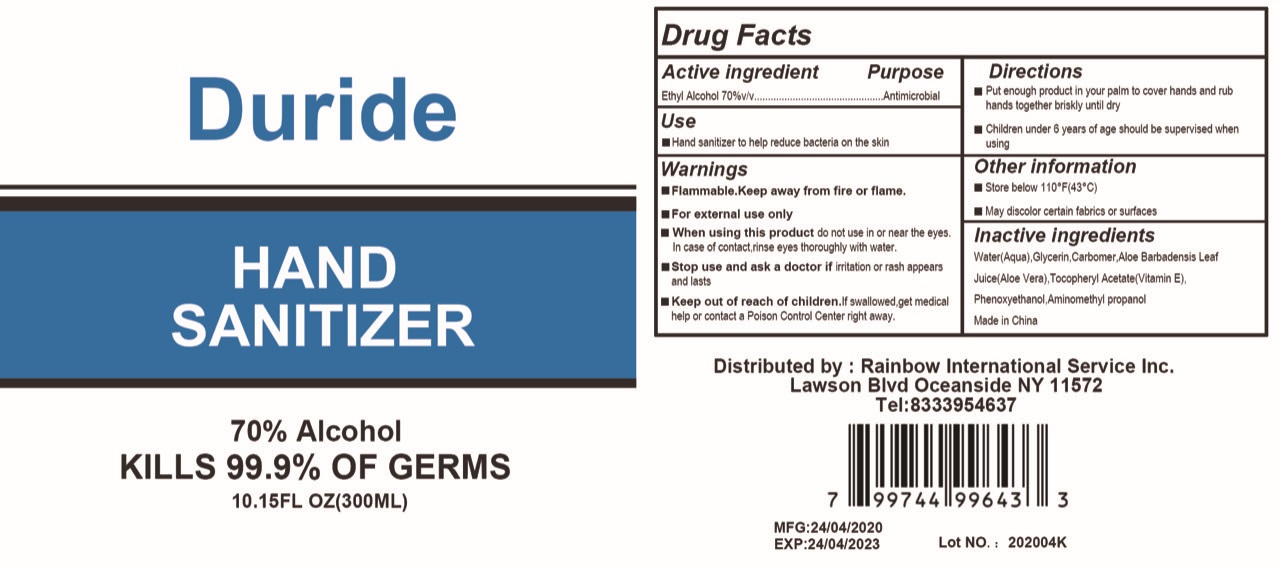 DRUG LABEL: Duride Hand Sanitizer
NDC: 77498-210 | Form: GEL
Manufacturer: Rainbow International Services Inc.
Category: otc | Type: HUMAN OTC DRUG LABEL
Date: 20200511

ACTIVE INGREDIENTS: ALCOHOL 210 mL/300 mL
INACTIVE INGREDIENTS: WATER; GLYCERIN; ALOE VERA LEAF; CARBOMER 940; AMINOMETHYLPROPANOL; .ALPHA.-TOCOPHEROL ACETATE

ACTIVE INGREDIENT

Alcohol

INACTIVE INGREDIENT

Water(Aqua), Glycerin, Carbomer, Aloe Barbadensis Leaf Juice(Aloe Vera), Tocopheryl Acetate(Vitamin E), Phenoxyethanol, Aminomethyl propanol

PURPOSE

Antimicrobial

INDICATIONS AND USAGE

■ Hand sanitizer to help reduce bacteria on the skin.

WARNINGS

■ Flammable. Keep away from fire or flame.

■ For external use only.

DO NOT USE

■ in children less than 2 months of age
■ on open skin wounds

When using this product do not use in or near the eyes. In case of contact, rinse eyes thoroughly with water.

Stop use and ask a doctor if irritation or rash appears and lasts

Keep out of reach of children. If swallowed, get medical help or contact a Poison Control Center right away.

STORAGE AND HANDLING

Store below 110℉(43℃)

DOSAGE AND ADMINISTRATION

Pump 1-2 times and rub it into your hand. For topical use only.